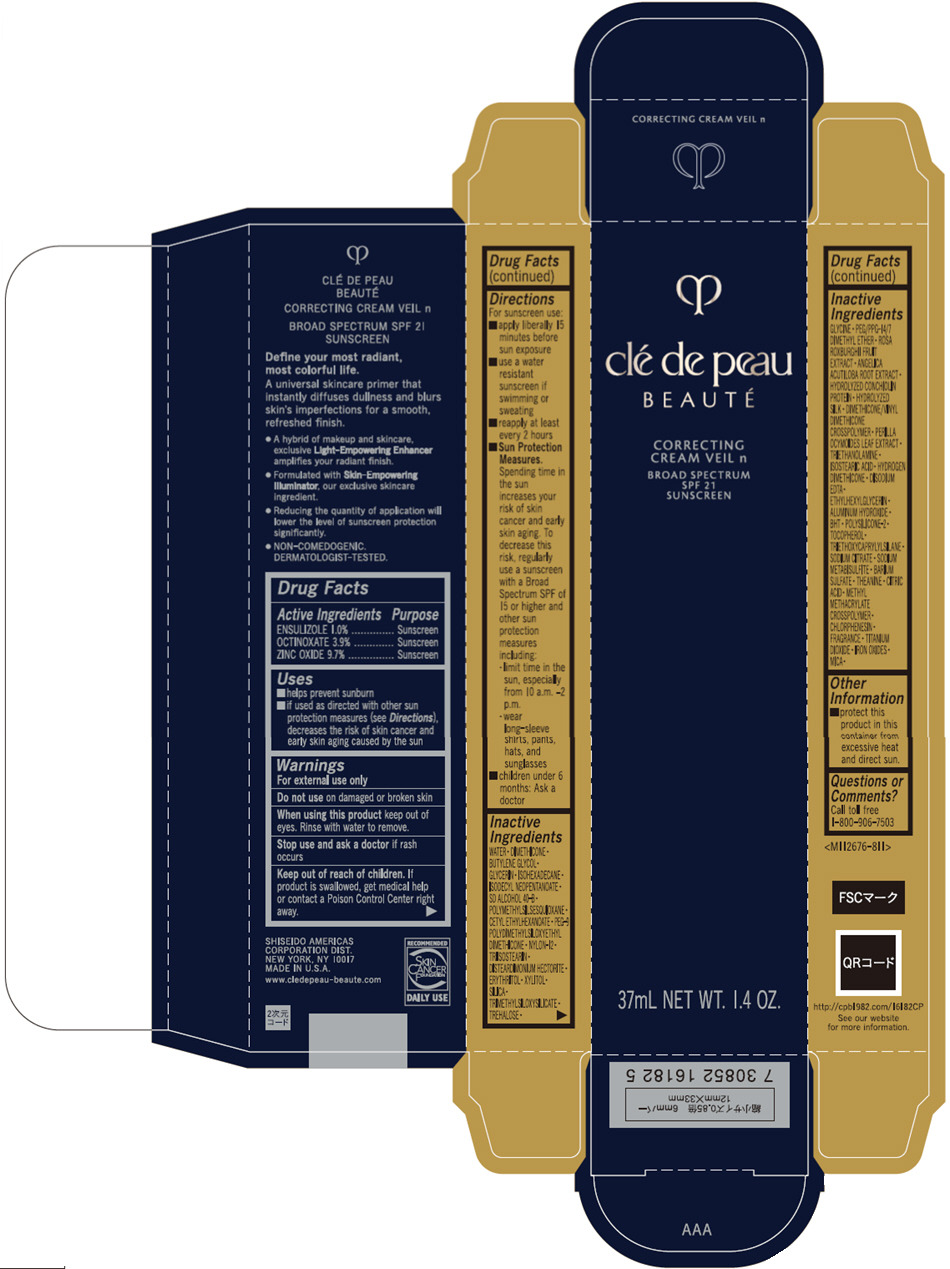 DRUG LABEL: cle de peau BEAUTE CORRECTING VEIL n M
NDC: 58411-892 | Form: CREAM
Manufacturer: SHISEIDO AMERICAS CORPORATION
Category: otc | Type: HUMAN OTC DRUG LABEL
Date: 20260105

ACTIVE INGREDIENTS: ENSULIZOLE 0.40552 g/37 mL; OCTINOXATE 1.581528 g/37 mL; ZINC OXIDE 3.933544 g/37 mL
INACTIVE INGREDIENTS: TOCOPHEROL; TRIMETHYLSILOXYSILICATE (M/Q 0.6-0.8); TREHALOSE; GLYCINE; PEG/PPG-14/7 DIMETHYL ETHER; ROSA ROXBURGHII FRUIT; ANGELICA ACUTILOBA ROOT; DIMETHICONE/VINYL DIMETHICONE CROSSPOLYMER (HARD PARTICLE); PERILLA FRUTESCENS LEAF; TROLAMINE; ISOSTEARIC ACID; HYDROGEN DIMETHICONE (13 CST); EDETATE DISODIUM; ETHYLHEXYLGLYCERIN; ALUMINUM HYDROXIDE; BUTYLATED HYDROXYTOLUENE; TRIETHOXYCAPRYLYLSILANE; SODIUM CITRATE, UNSPECIFIED FORM; SODIUM METABISULFITE; BARIUM SULFATE; THEANINE; CITRIC ACID MONOHYDRATE; CHLORPHENESIN; TITANIUM DIOXIDE; FERRIC OXIDE RED; FERRIC OXIDE YELLOW; FERROSOFERRIC OXIDE; MICA; WATER; DIMETHICONE; BUTYLENE GLYCOL; GLYCERIN; ISOHEXADECANE; ISODECYL NEOPENTANOATE; ALCOHOL; POLYMETHYLSILSESQUIOXANE (11 MICRONS); CETYL ETHYLHEXANOATE; PEG-9 POLYDIMETHYLSILOXYETHYL DIMETHICONE; NYLON-12; TRIISOSTEARIN; DISTEARDIMONIUM HECTORITE; ERYTHRITOL; XYLITOL; SILICON DIOXIDE

clé de peau BEAUTÉ CORRECTING CREAM VEIL n M

Drug Facts

ACTIVE INGREDIENT

Active ingredients | Purpose
ENSULIZOLE 1.0% | Sunscreen
OCTINOXATE 3.9% | Sunscreen
ZINC OXIDE 9.7% | Sunscreen

Uses

- helps prevent sunburn
- if used as directed with other sun protection measures (see Directions), decreases the risk of skin cancer and early skin aging caused by the sun

Warnings

For external use only

Do not useon damaged or broken skin

WHEN USING

When using this productkeep out of eyes. Rinse with water to remove.

Stop use and ask a doctorif rash occurs.

Keep out of reach of children.If product is swallowed, get medical help or contact a Poison Control Center right away.

Directions

For sunscreen use:

- apply liberally 15 minutes before sun exposure
- use a water resistant sunscreen if swimming or sweating
- reapply at least every 2 hours
- Sun Protection Measures. Spending time in the sun increases your risk of skin cancer and early skin aging. To decrease this risk, regularly use a sunscreen with a Broad Spectrum SPF of 15 or higher and other sun protection measures including:
  - limit time in the sun, especially from 10 a.m. – 2 p.m.
  - wear long-sleeve shirts, pants, hats, and sunglasses
- children under 6 months: Ask a doctor

Inactive Ingredients

WATER∙DIMETHICONE∙BUTYLENE GLYCOL∙GLYCERIN∙ISOHEXADECANE∙ISODECYL NEOPENTANOATE∙SD ALCOHOL 40-B∙POLYMETHYLSILSESQUIOXANE∙CETYL ETHYLHEXANOATE∙PEG-9 POLYDIMETHYLSILOXYETHYL DIMETHICONE∙NYLON-12∙TRIISOSTEARIN∙DISTEARDIMONIUM HECTORITE∙ERYTHRITOL∙XYLITOL∙SILICA∙TRIMETHYLSILOXYSILICATE∙TREHALOSE∙GLYCINE∙PEG/PPG-14/7 DIMETHYL ETHER∙ROSA ROXBURGHII FRUIT EXTRACT∙ANGELICA ACUTILOBA ROOT EXTRACT∙HYDROLYZED CONCHIOLIN PROTEIN∙HYDROLYZED SILK∙DIMETHICONE/VINYL DIMETHICONE CROSSPOLYMER∙PERILLA OCYMOIDES LEAF EXTRACT∙TRIETHANOLAMINE∙ISOSTEARIC ACID∙HYDROGEN DIMETHICONE∙DISODIUM EDTA∙ETHYLHEXYLGLYCERIN∙ALUMINUM HYDROXIDE∙BHT∙POLYSILICONE-2∙TOCOPHEROL∙TRIETHOXYCAPRYLYLSILANE∙SODIUM CITRATE∙SODIUM METABISULFITE∙BARIUM SULFATE∙THEANINE∙CITRIC ACID∙METHYL METHACRYLATE CROSSPOLYMER∙CHLORPHENESIN∙FRAGRANCE∙TITANIUM DIOXIDE∙IRON OXIDES∙MICA∙

Other information

- protect this product in this container from excessive heat and direct sun.

Questions or comments?

Call toll free 1-800-906-7503

PRINCIPAL DISPLAY PANEL - 37 mL Tube Carton

clé de peau
BEAUTÉ

CORRECTING
CREAM VEIL n

BROAD SPECTRUM
SPF 21
SUNSCREEN

37mL NET WT. 1.4 OZ.